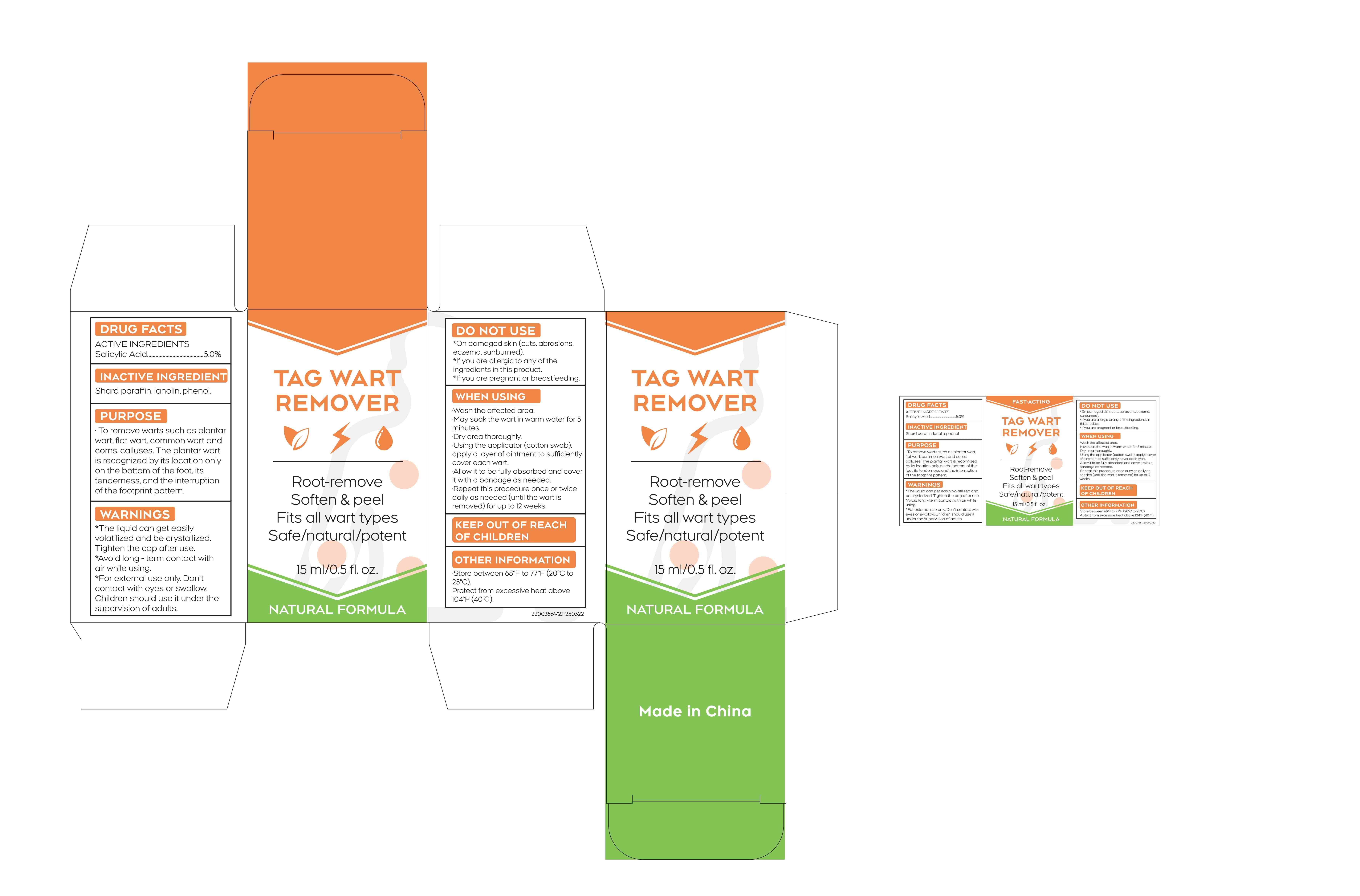 DRUG LABEL: TAG WART REMOVER
NDC: 84023-116 | Form: LIQUID
Manufacturer: Shenzhen Yangan Technology Co., Ltd.
Category: otc | Type: HUMAN OTC DRUG LABEL
Date: 20250420

ACTIVE INGREDIENTS: SALICYLIC ACID 5 mg/100 mL
INACTIVE INGREDIENTS: PARAFFIN; PHENOL; LANOLIN

15ml

ACTIVE INGREDIENT

Salicylic Acid.......................................5.0%

INACTIVE INGREDIENT

Shard paraffin, lanolin, phenol.

PURPOSE

To remove warts such as plantar wart, flat wart, common wart and corns, calluses. The plantar wart is recognized by its location only on the bottom of the foot, its tenderness, and the interruption of the footprint pattern.

DO NOT USE

· On damaged skin (cuts, abrasions, eczema, sunburn).

· If you are allergic to any of the ingredients in this product.

· If you are pregnant or breastfeeding.

WHEN USING

·Wash the affected area.

·May soak the wart in warm water for 5 minutes.

·Dry area thoroughly.

·Using the applicator (cotton swab), apply a layer of ointment to sufficiently cover each wart.

·Allow it to be fully absorbed and cover it with a bandage as needed.

·Repeat this procedure once or twice daily as needed (until the wart is removed) for up to 12 weeks.

WARNINGS

The liquid can get easily volatilized and be crystallized. Tighten the cap after use.

·Avoid long - term contact with air while using.

·For external use only. Don't contact with eyes or swallow. Children should use it under the supervision of adults.

DOSAGE AND ADMINISTRATION

Repeat this procedure once or twice daily as needed (until the wart is removed) for up to 12 weeks.

INDICATIONS AND USAGE

Wash the affected area.
May soak the wart in warmwater for 5 minutes.
Dry area thoroughly.
Using the applicator(cottonswab）apply a layer ofointment to sufficiently cover each wart
Allow it to fully absorb andcover it with a bandage asneeded.
Repeat this procedure onceor twice daily as needed (until the wart is removed) for upto12weeks

OTHER SAFETY INFORMATION

Store between 68°F to 77°F (20°C to 25°C).

Protect from excessive heat above 104°F (40℃).

KEEP OUT OF REACH OF CHILDREN